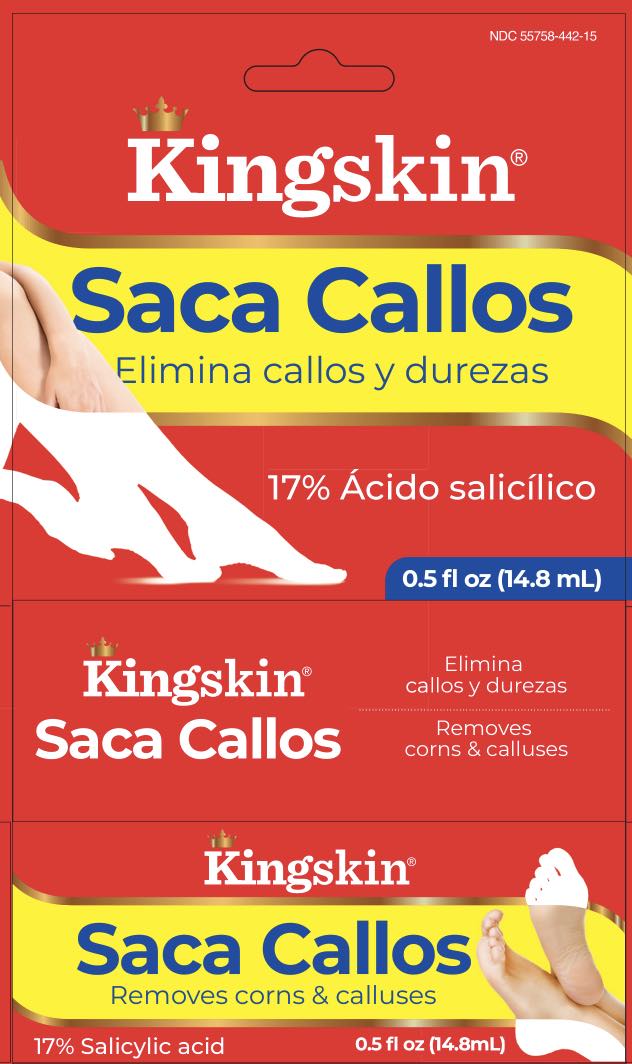 DRUG LABEL: Kingskin Saca Callos
NDC: 55758-442 | Form: LIQUID
Manufacturer: Pharmadel
Category: otc | Type: HUMAN OTC DRUG LABEL
Date: 20251204

ACTIVE INGREDIENTS: SALICYLIC ACID 17 g/100 mL
INACTIVE INGREDIENTS: ETHER; ALCOHOL; CAMPHOR (SYNTHETIC)

Kingskin Saca Callos (WP)

Active ingredient and Purpose

Active ingredient | Purpose
Clotrimazole 1% | Antifungal

Uses

- for the removal of corns and calluses
- relieves pain by removing corns and calluses

Warnings

FOR EXTERNAL USE ONLY.

Flammable: Keep away from fire or flame.

Do not use

- this product on irritated skin, on any area that is infected or reddened, if you are a diabetic, or if you have poor blood circulation

When using this product

- if it gets into the eye, flush with water for 15 minutes
- avoid inhaling vapors

Stop use and ask a doctor or podiatrist if

- discomfort persists

If pregnant or lactating

consult a doctor before using this product.

KEEP OUT OF REACH OF CHILDREN.

In case of accidental ingestion, get medical help or contact a Poison Control Center immediately.

Directions

- wash affected area and dry thoroughly
- apply a small amount at a time with applicator to sufficiently cover each corn/callus
- let dry
- repeat this procedure once or twice daily as needed up to 14 days (until corn/callus is removed)
- may soak corn/callus in warm water for 5 minutes to assist in removal

Other information

- cap bottle tightly and store at room temperature away from heat
- do not use if seal over cap is torn or missing

Inactive ingredients

alcohol, camphor, ether

Questions?

+1-866-359-3478 (M-F) 9AM-5PM EST or www.pharmadel.com

Distributed by/ Distribuido por:

PHARMADEL LLC

New Castle, DE 19720 • www.pharmadel.com

+1-866-359-3478

Made in India / Hecho en India